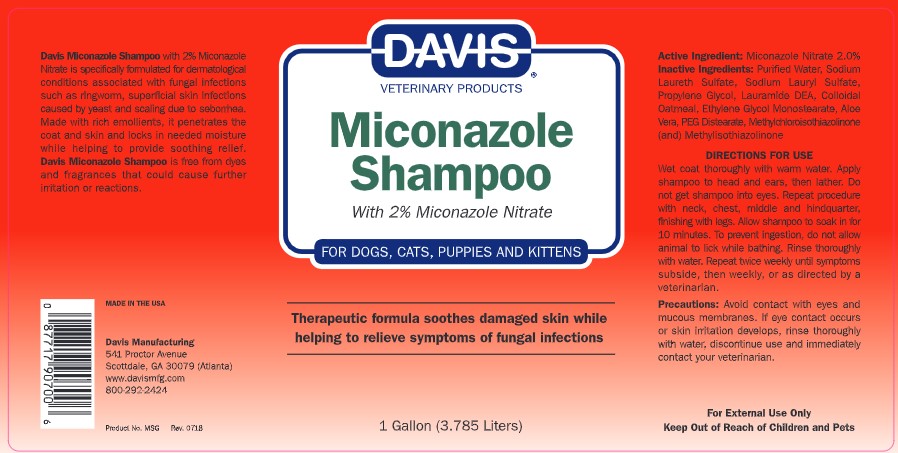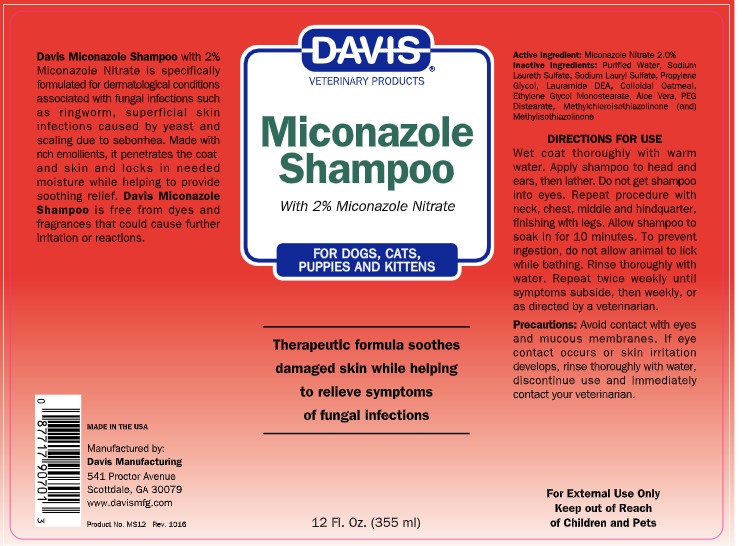 DRUG LABEL: Davis Miconazole
NDC: 62570-070 | Form: SHAMPOO
Manufacturer: Davis Manufacturing and Packaging Inc
Category: animal | Type: OTC ANIMAL DRUG LABEL
Date: 20191107

ACTIVE INGREDIENTS: MICONAZOLE NITRATE 2 g/100 g
INACTIVE INGREDIENTS: WATER; SODIUM LAURETH SULFATE; SODIUM LAURYL SULFATE; OATMEAL; PROPYLENE GLYCOL 1,2-DISTEARATE; PROPYLENE GLYCOL; METHYLCHLOROISOTHIAZOLINONE/METHYLISOTHIAZOLINONE MIXTURE; LAURIC DIETHANOLAMIDE; GLYCOL STEARATE; ALOE VERA LEAF

Miconazole Shampoo

DESCRIPTION

Davis Miconazole Shampoo with 2% Miconazole Nitrate is specifically formulated for dermatological conditions associated with fungal infections such as ringworm, superficial skin infections caused by yeast and scaling due to seborrhea. Made with rich emollients, it penetrates the coat and skin and locks in needed moisture while helping to provide soothing relief. Davis Miconazole Shampoo is free from dyes and fragrances that could cause further irritation or reactions.

MADE IN THE USA

Davis Manufacturing

541 Proctor Avenue

Scottdale, GA 30079

www.davismfg.com

Product No. MS12 Rev 0712

Active Ingredient: Miconazole Nitrate 2.0%

INACTIVE INGREDIENT

Inactive Ingredients: Purified Water, Sodium Laureth Sulfate, Sodium Lauryl Sulfate, Propylene Glycol, Lauramide DEA, Colloidal Oatmeal, Ethylene Glycol Monostearate, Aloe Vera, PEG Distearate, Methylchloroisothiazolinone (and) Methylisothiazolinone

INSTRUCTIONS FOR USE

DIRECTIONS FOR USE Wet coat thoroughly with warm water. Apply shampoo to head and ears, then lather. Do not get shampoo into eyes. Repeat procedure with neck, chest, middle and hindquarter, finishing with legs. Allow shampoo to soak in for 10 minutes. To prevent ingestion, do not allow animal to lick while bathing. Rinse thoroughly with water. Repeat twice weekly until symptoms subside, then weekly, or as directed by a veterinarian.

If desired follow the Davis Miconazole Shampoo bath with one using Davis Chlorhexidine Shampoo or make your own Miconazole/Chlorhexidine Shampoo by premixing Davis Miconazole shampoo and Davis Chlorhexidine Shampoo.

PRECAUTIONS

Precautions: Avoid contact with eyes and mucous membranes. If eye contact occurs or skin irritation develops, rinse thoroughly with water, discontinue use and immediately contact your veterinarian.

PACKAGE LABEL

Davis Veterinary Products
Miconazole Shampoo
With 2% Miconazole Nitrate
For Dogs, Cats, Puppies and Kittens
Therapeutic formula includes Colloidal Oatmeal to soothe damaged skin while helping to relieve symptoms of fungal infections
1 Gallon (3.785 Liters)

PACKAGE LABEL

Davis Veterinary Products
Miconazole Shampoo
With 2% Miconazole Nitrate
For Dogs, Cats, Puppies and Kittens
Therapeutic formula includes Colloidal Oatmeal to soothe damaged skin while helping to relieve symptoms of fungal infections